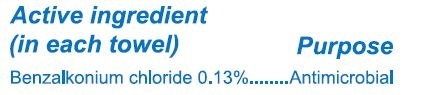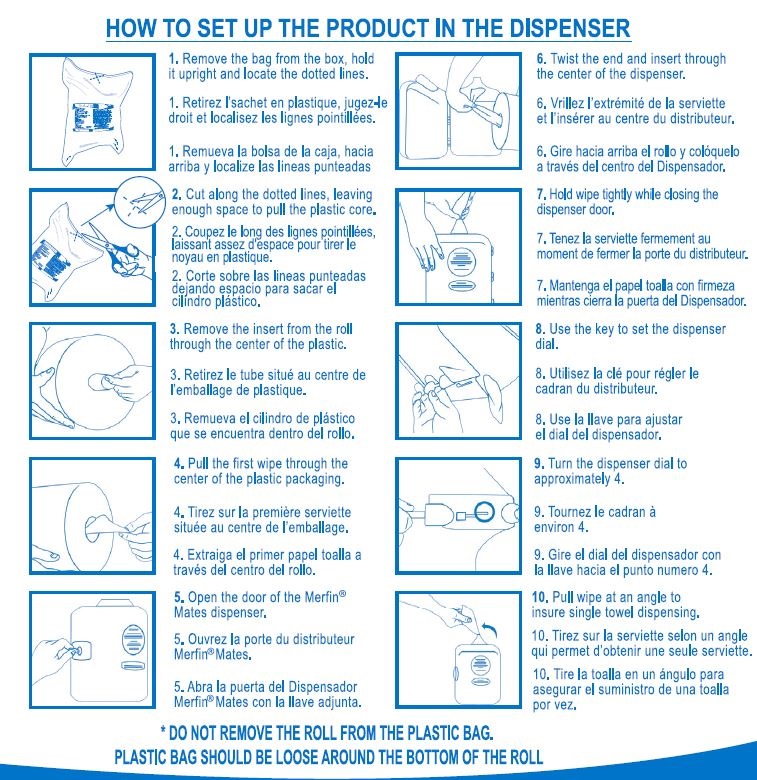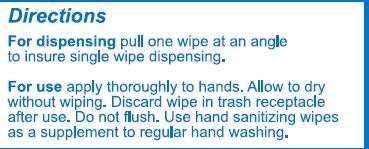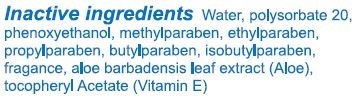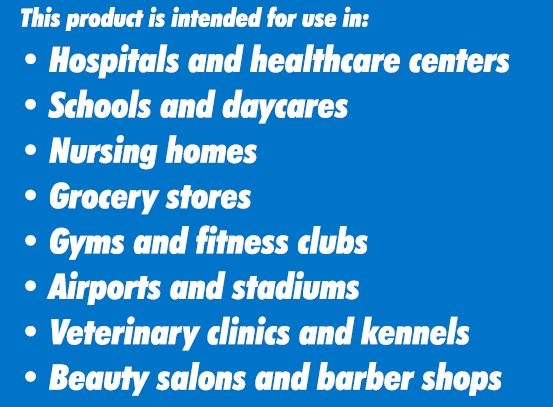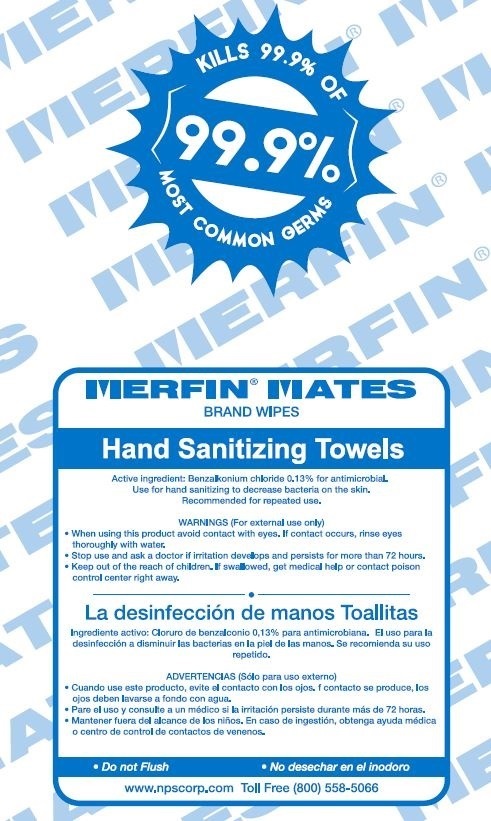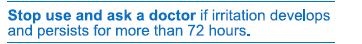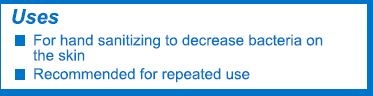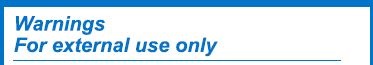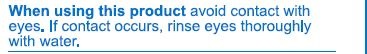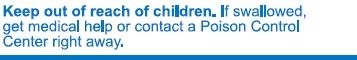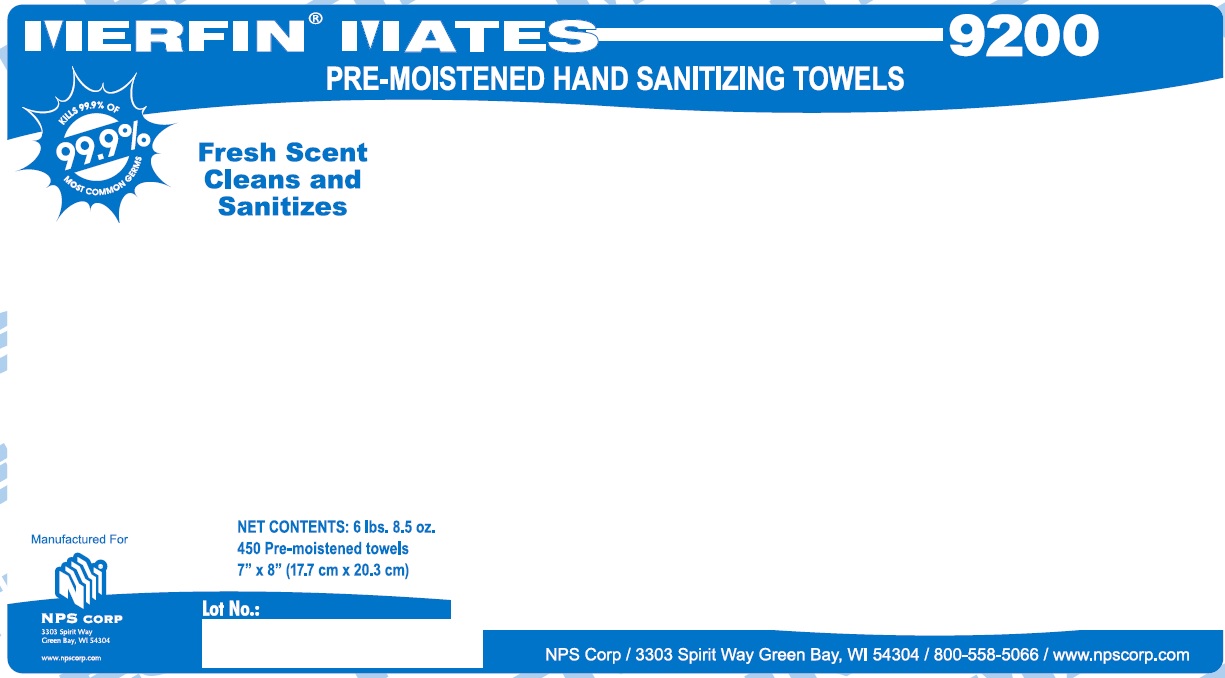 DRUG LABEL: Merfin Mates Hand Sanitizing Towels
NDC: 67313-9200 | Form: CLOTH
Manufacturer: NPS Holdings LLC
Category: otc | Type: HUMAN OTC DRUG LABEL
Date: 20210331

ACTIVE INGREDIENTS: BENZALKONIUM CHLORIDE 0.13 g/1 1
INACTIVE INGREDIENTS: METHYLPARABEN; PROPYLPARABEN; SORBIC ACID; WATER; ALOE VERA LEAF; ALCOHOL; POLYSORBATE 20; ISOBUTYLPARABEN; BUTYLPARABEN; .ALPHA.-TOCOPHEROL ACETATE; ANHYDROUS CITRIC ACID; PHENOXYETHANOL; ETHYLPARABEN

INDICATIONS AND USAGE

This product is intended for use in:

- Hospitals and healthcare centers
- Schools and daycares
- Nursing homes
- Grocery stores
- Gyms and fitness clubs
- Airports and stadiums
- Veterinary clinics and kennels
- Beauty salons and barber shops

Active ingredient

(in each towel)

Purpose

Benzalkonium chloride 0.13%........Antimicrobial

Uses

- For hand sanitizing to decrease bacteria on the skin
- Recommended for repeated use

Warnings

For external use only

When using this product avoid contact with

eyes. If contact occurs, rinse eyes thoroughly

with water.

Stop use and ask a doctor if irritation develops

and persists for more than 72 hours.

Keep out of reach of children. If swallowed,

get medical help or contact a Poison Control

Center right away.

Directions

For dispensing pull one towel at an angle

to insure single towel dispensing.

For use apply thoroughly to hands. Allow to dry

without wiping. Discard towel in trash receptacle

after use. Do not flush. Use hand sanitizing towels

as a supplement to regular hand washing.

Inactive ingredients Water, Alcohol Denat,

Aloe Barbadensis Leaf Juice, Polysorbate 20,

Tocopheryl Acetate, Sorbic Acid, Citric Acid,

Methylparaben, Propylparaben, Ethylparaben,

Butylparaben, Isobutylparaben, Phenoxyethanol,

Fragrance

ASSEMBLY OR INSTALLATION INSTRUCTIONS

HOW TO SET UP THE PRODUCT IN THE DISPENSER

1. Remove the bag from the box, hold it upright and locate the dotted lines.
2. Cut along the dotted lines, leaving enough space to pull the plastic core.
3. Remove the insert from the roll through the center of the plastic.
4. Pull the first wipe through the center of the plastic packaging.
5. Open the door of the Merfin® Mates dispenser.
6. Twist the end and insert through the center of the dispenser.
7. Hold wipe tightly while closing the dispenser door.
8. Use the key to set the dispenser dial.
9. Turn the dispenser dial to approximately 4.
10. Pull wipe at an angle to insure single towel dispensing.

*DO NOT REMOVE THE ROLL FROM THE PLASTIC BAG.

PLASTIC BAG SHOULD BE LOOSE AROUND THE BOTTOM OF THE ROLL

DESCRIPTION

KILLS 99.9% OF

99.9%

MOST COMMON GERMS

MERFIN® MATES

BRAND WIPES

Hand Sanitizing Wipes

Active Ingredient: Benalkonium chloride 0.13% for anti-microbial.

Use for hand sanitizing to decrease bacteria on the skin.

Recommended for repeated use.

WARNINGS (For external use only)

When using this product avoid contact with eyes. If contact occurs, rinse eyes
thoroughly with water.
Stop use and ask a doctor if irritation develops and persists for more than 72 hours.
Keep out of reach of children. If swallowed, get medical help or contact poison
control center right away.

______________________________________________________________________________________

La desinfección de manos Toallitas

Ingrediente activo: Cloruro de benzalconio 0,13% para anti-microbiana. El uso para la

desinfección a disminuir las bacterias en la piel de las manos. Se recomienda su uso

repetido.

ADVERTENCIAS (Sólo para uso externo)

Cuando use este producto, evite el contacto con los ojos. f contacto se produce, los ojos deben lavarse a fondo con agua.
Pare el uso y consulte a un médico si la irritación persiste durante más de 72 horas.
Mantener fuera del alcance de los niños. En caso de ingestión, obtenga ayuda médica o centro de control de contactos de venenos.

Do not Flush
Do desechar en el inodoro

www.npscorp.com Toll Free (800) 558-5066

PACKAGE LABEL

MERFIN® MATES 9200

PRE-MOISTENED HAND SANITIZING TOWELS

KILLS 99.9% OF MOST COMMON GERMS

Fresh Scent Cleans and

Sanitizes

NET CONTENTS: 6lbs. 8.5 oz.

450 Pre-moistened towels

7" x 8" (17.7 cm x 20.3 cm)

Manufactured For

NPS CORP

3303 Spirit Way

Green Bay, WI 54302

www.npscorp.com

Lot No.: ___________

NPS Corp / 3303 Spirit Way Green Bay, WI 54304 / 800-558-5066 / npscorp.com